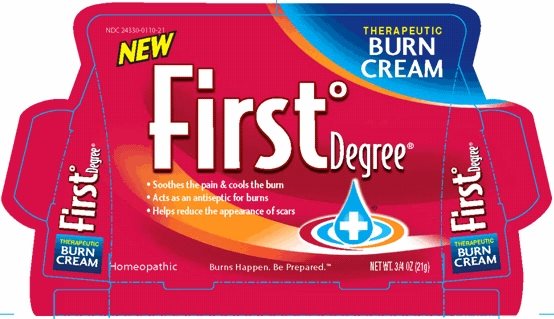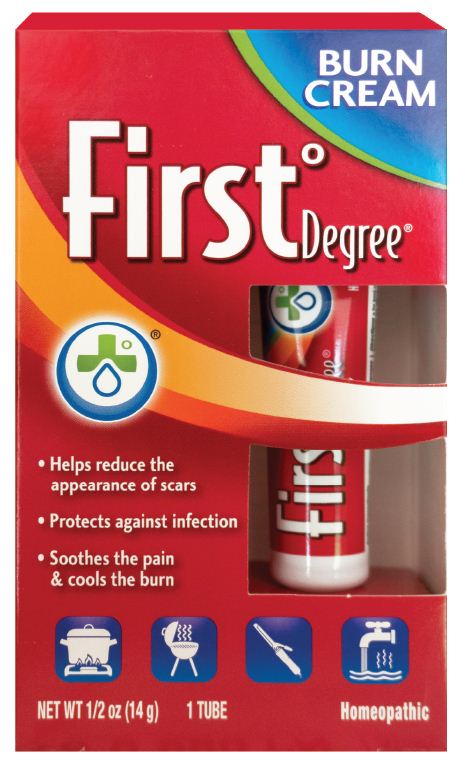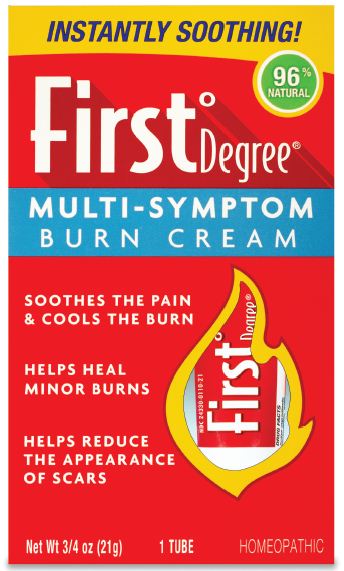 DRUG LABEL: First Degree
NDC: 24330-110 | Form: TINCTURE
Manufacturer: Welmedix LLC
Category: homeopathic | Type: HUMAN OTC DRUG LABEL
Date: 20150812

ACTIVE INGREDIENTS: CALENDULA OFFICINALIS FLOWERING TOP 1 [hp_Q]/0.1 g; ECHINACEA ANGUSTIFOLIA 1 [hp_Q]/0.1 g; LYTTA VESICATORIA 3 [hp_X]/0.1 g
INACTIVE INGREDIENTS: SHEA BUTTER; HYDROGENATED POLYDECENE (550 MW); ISOPROPYL MYRISTATE; LANOLIN; METHYLPARABEN; PROPYLPARABEN; WATER; TRIDECETH-10

First°Degree® Burn Cream

Active ingredients

Calendula officinalis TINC HPUS

Cantharis vesicatoria 3X HPUS

Echinacea angustifolia TINC HPUS

The letters ‘HPUS’ indicate that the active ingredients are officially monographed in the Homeopathic Pharmacopoeia of the United States. TINC and 3X are homeopathic dilutions: see www.firstdegree.com for details.

Purposes

wound healing, superficial burns and scalds

burns, scalds, rawness, burning pain

itching, burning, irritation from insect bites

Uses

Temporarily relieves symptoms such as minor skin pain, rawness and itching due to:

- minor burns
- insect bites
- minor scrapes
- scalds

Product Uses are based on the Homeopathic Materia Medica, and have not been evaluated by the Food and Drug Administration.

Warnings

For external use only

Do not use

- if you have an allergy or hypersensitivity to any ingredients or if you have had a prior reaction to this product
- over large areas of the body
- on deep or puncture wounds
- on animal bites
- on serious burns, cuts or scrapes

When using this product

do not get into eyes

Stop use and ask a doctor if

- condition worsens
- symptoms last more than 7 days or clear up and occur again within a few days

If pregnant or breast feeding

ask a health professional before use.

Keep out of reach of children.

If swallowed, get medical help or contact a Poison Control Center right away.

Directions

- for best results, apply immediately to affected area
- adults and children 2 years of age and older: apply to affected area 2-3 times a day, as needed, or as directed by your doctor
- children under 2 years of age: consult a doctor

Other information

store at 15-30°C (59-86°F)

Inactive ingredients

butyrospermum parkii (shea butter), C18-22 hydroxyalkyl hydroxypropyl guar, hydrogenated polydecene, isopropyl myristate, lanolin, methylparaben, propylparaben, purified water, sodium polyacryloyldimethyl taurate, trideceth-10

Questions or comments?

Call 1-888-565-2876 Monday through Friday, 9am-5pm

Principal Display Panel - First°Degree® Therapeutic Burn Cream

NEW

THERAPEUTIC
BURN
CREAM

First°Degree®

NDC 24330-0110-21

- Soothes the pain & cools the burn
- Acts as an antiseptic for burns
- Helps reduce the appearance of scars

Homeopathic

Burns Happen. Be Prepared.™

NET WT. 3/4 OZ (21g)

Carton Label - First°Degree® Therapeutic Burn Cream

Principal Display Panel - First°Degree® Burn Cream

BURN
CREAM

First°Degree®

- Helps reduce the
  appearance of scars
- Protects against infection
- Soothes the pain
  & cools the burn

NET WT 1/2 oz (14 g)

1 TUBE

Homeopathic

Carton Label - First°Degree® Burn Cream

Principal Display Panel – First°Degree® Multi-Symptom Burn Cream

INSTANTLY SOOTHING!

96% NATURAL

First°Degree®

MULTI-SYMPTOM
BURN CREAM

SOOTHES THE PAIN
& COOLS THE BURN

HELPS HEAL
MINOR BURNS

HELPS REDUCE
THE APPEARANCE
OF SCARS

Net Wt 3/4 oz (21g)

1 TUBE

HOMEOPATHIC

Carton Label - First°Degree® Multi-Symptom Burn Cream